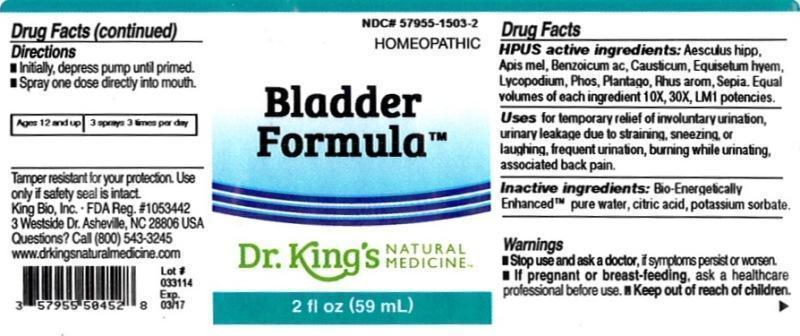 DRUG LABEL: Bladder Formula
NDC: 57955-1503 | Form: LIQUID
Manufacturer: King Bio Inc.
Category: homeopathic | Type: HUMAN OTC DRUG LABEL
Date: 20160308

ACTIVE INGREDIENTS: HORSE CHESTNUT 10 [hp_X]/59 mL; APIS MELLIFERA 10 [hp_X]/59 mL; BENZOIC ACID 10 [hp_X]/59 mL; CAUSTICUM 10 [hp_X]/59 mL; EQUISETUM HYEMALE 10 [hp_X]/59 mL; LYCOPODIUM CLAVATUM SPORE 10 [hp_X]/59 mL; PHOSPHORUS 10 [hp_X]/59 mL; PLANTAGO MAJOR 10 [hp_X]/59 mL; RHUS AROMATICA ROOT BARK 10 [hp_X]/59 mL; SEPIA OFFICINALIS JUICE 10 [hp_X]/59 mL
INACTIVE INGREDIENTS: WATER; CITRIC ACID MONOHYDRATE; POTASSIUM SORBATE

Bladder Formula™

ACTIVE INGREDIENT

Drug Facts__________________________________________________________________________________________________________

HPUS activeingredients: Aesculus hippocastanum, Apis mellifica, Benzoicum acidum, Causticum, Equisetum hyemale, Lycopodium clavatum, Phosphorus, Plantago major, Rhus aromatica, Sepia. Equal volumes of each ingredient in 10X, 30X, LM1 potencies.

INDICATIONS AND USAGE

Uses for temporary relief of involuntary urination, urinary leakage due to straining, sneezing, or laughing, frequent urination, burning while urinating, associated back pain.

Inactive Ingredients:

Bio-Energetically Enhanced™ pure water, citric acid and potassium sorbate.

Warnings

- Stop use and ask your doctor if symptoms persist or worsen.
- If pregnant or breast-feeding, ask a healthcare professional before use.

- Keep out of reach of children.

Directions

- Initially, depress pump until primed.
- Spray one dose directly into mouth.
- Ages 12 and up: 3 sprays 3 times per day.

OTHER SAFETY INFORMATION

Tamper resistant for your protection. Use only if safety seal is intact.

PURPOSE

Uses for temporary relief of:

- involuntary urination
- urinary leakage due to straining, sneezing, or laughing
- frequent urination
- burning while urinating
- associated back pain